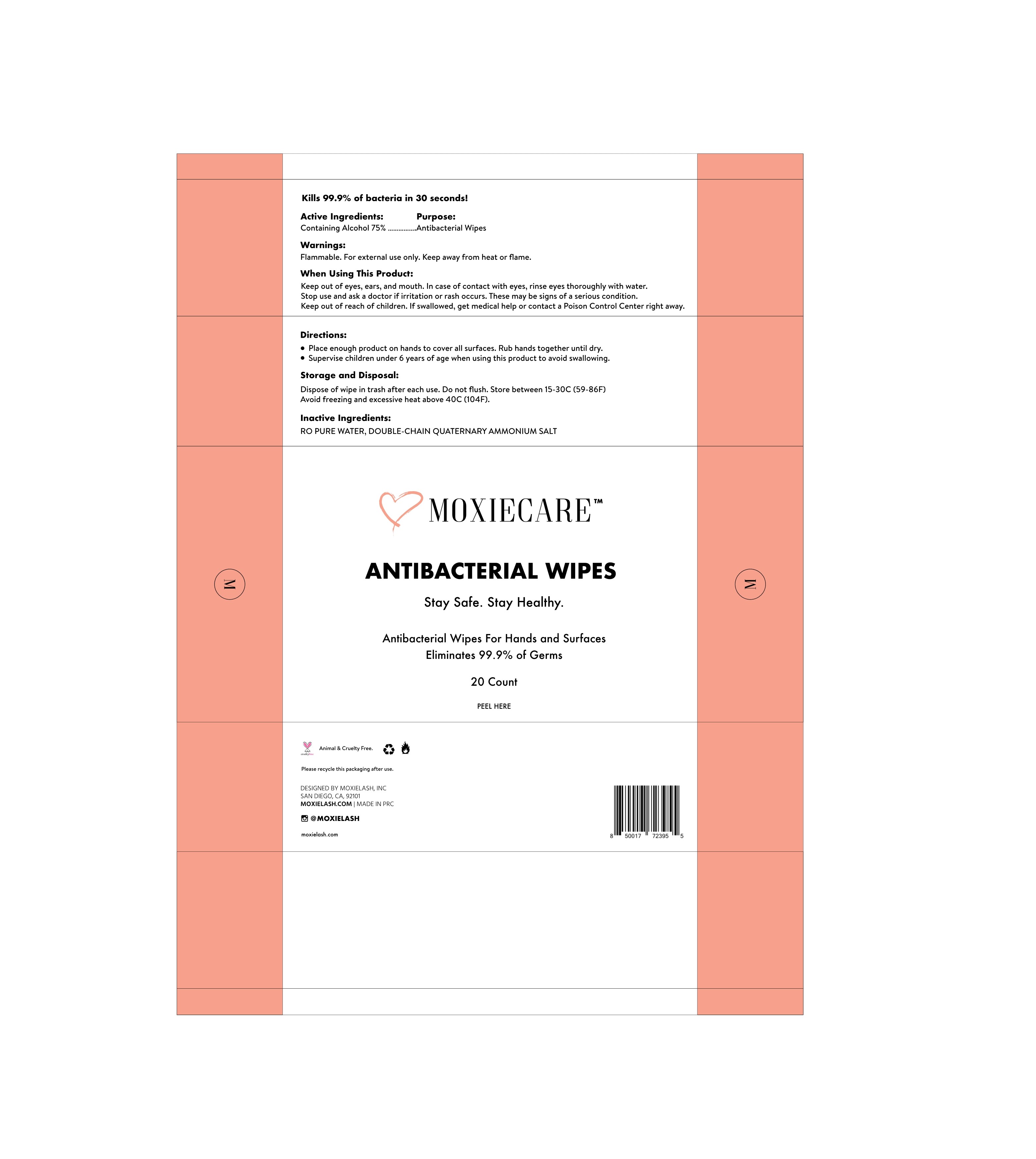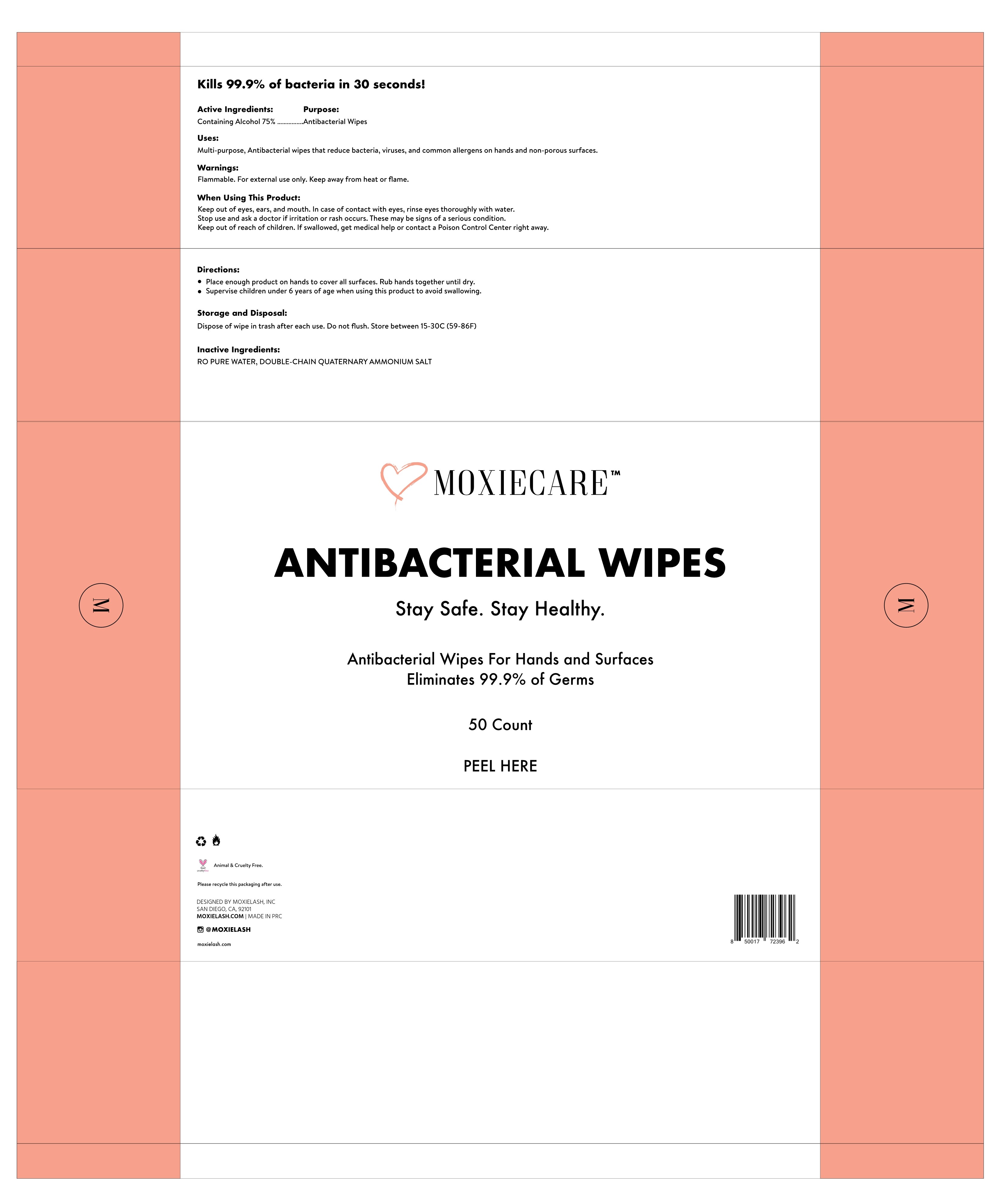 DRUG LABEL: Moxiecare Antibacterial Wipes
NDC: 75428-002 | Form: CLOTH
Manufacturer: Shandong Baihe Toilet Products Co.,Ltd
Category: otc | Type: HUMAN OTC DRUG LABEL
Date: 20200430

ACTIVE INGREDIENTS: ALCOHOL 75 1/100 1
INACTIVE INGREDIENTS: AMMONIUM HYPOPHOSPHITE; WATER

Active Ingredient(s)

Containingl Alcohol 75%

Purpose

Purpose: Antibacterial Wipes

Use

Multi-purpose, Antibacterial wipes that reduce bacteria, viruses, and common allergens on hands and non-porous surfaces.

Warnings

Flammable. For external use only. Keep away from heat or flame.

Do not use

- in children less than 2 months of age
- on open skin wounds

WHEN USING

Kepp out and ask ears, and mouth. In case of contact with eyes, rinse eyes thoroughly.Keep out owith waterctor if irritation or rash occurs. These may be signs of a serious conditionout of reach of children. If swallowed, get medical help or contact a Poison Control Center right away

Stop use and ask a doctor if irritation or rash occurs. These may be signs of a serious condition.

Keep out of reach of children. If swallowed, get medical help or contact a Poison Control Center right away.

Directions

- Place enough product on hands to cover all surfaces. Rub hands together until dry.Supervise children under 6 years of age when using this product to avoid swallowing.

Other information

- Dispose of wipe in trash after each use. Do not flush Store between 15-30C(59-86F)Avoid freezing and excessive heat above 40C(104F).

Inactive ingredients

RO PURE WATER, DOUBLE-CHAIN QUATERNARY AMMONIUM SALT